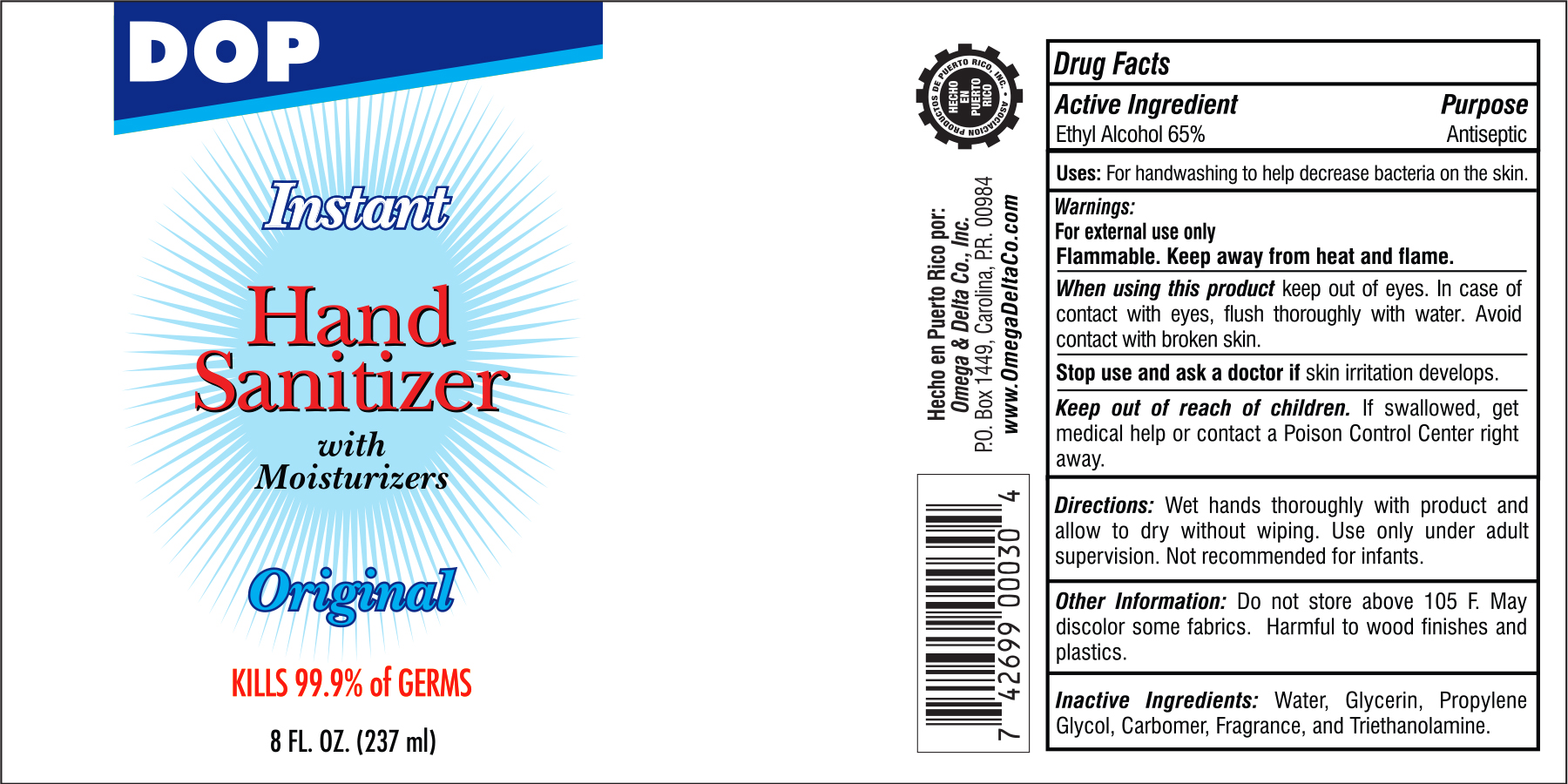 DRUG LABEL: DOP Hand Sanitizer
NDC: 51048-027 | Form: GEL
Manufacturer: Omega & Delta Co
Category: otc | Type: HUMAN OTC DRUG LABEL
Date: 20201006

ACTIVE INGREDIENTS: ALCOHOL 65 mL/100 mL
INACTIVE INGREDIENTS: WATER; GLYCERIN; PROPYLENE GLYCOL; CARBOMER 940; TROLAMINE; FRAGRANCE LEMON ORC2001060

DOP Instant Hand Sanitizer Original

Drug Facts

Active Ingredient

Ethyl Alcohol 65%

Purpose

Antiseptic

INDICATIONS AND USAGE

Uses: For handwashing to decrease bacteria on the skin.

Warnings:

For external use only

Flammable. Keep away from heat and flame.

When using this product keep out of eye. In case of contact with eyes, flush thoroughly with water. Avoid contact with broken skin.

Stop use and ask a doctor if skin irritation develops.

Keep out of reach of children. If swallowed, get medical help or contact a Poison Control center right away.

DOSAGE AND ADMINISTRATION

Directions: Wet hands thoroughly with product and allow to dry without wiping. Use only under adult supervision. Not recommended for infants.

Other Information: Do not store above 105o F. May discolor some fabrics. Harmful to wood finishes and plastics.

INACTIVE INGREDIENT

Inactive Ingredients: Water, Glycerin, propylene Glycol, carbomer, Fragrance, and Triethanolamine

Hecho en Puerto Rico por:

Omega & Delta Co., Inc.P.O. Box 1449, Carolina, P.R. 00984

PACKAGE LABEL

DOP

Instant

Hand

Sanitizer

with

Moisturizers

Original

KILLS 99.9% of GERMS

8 FL. OZ. (237 ml)